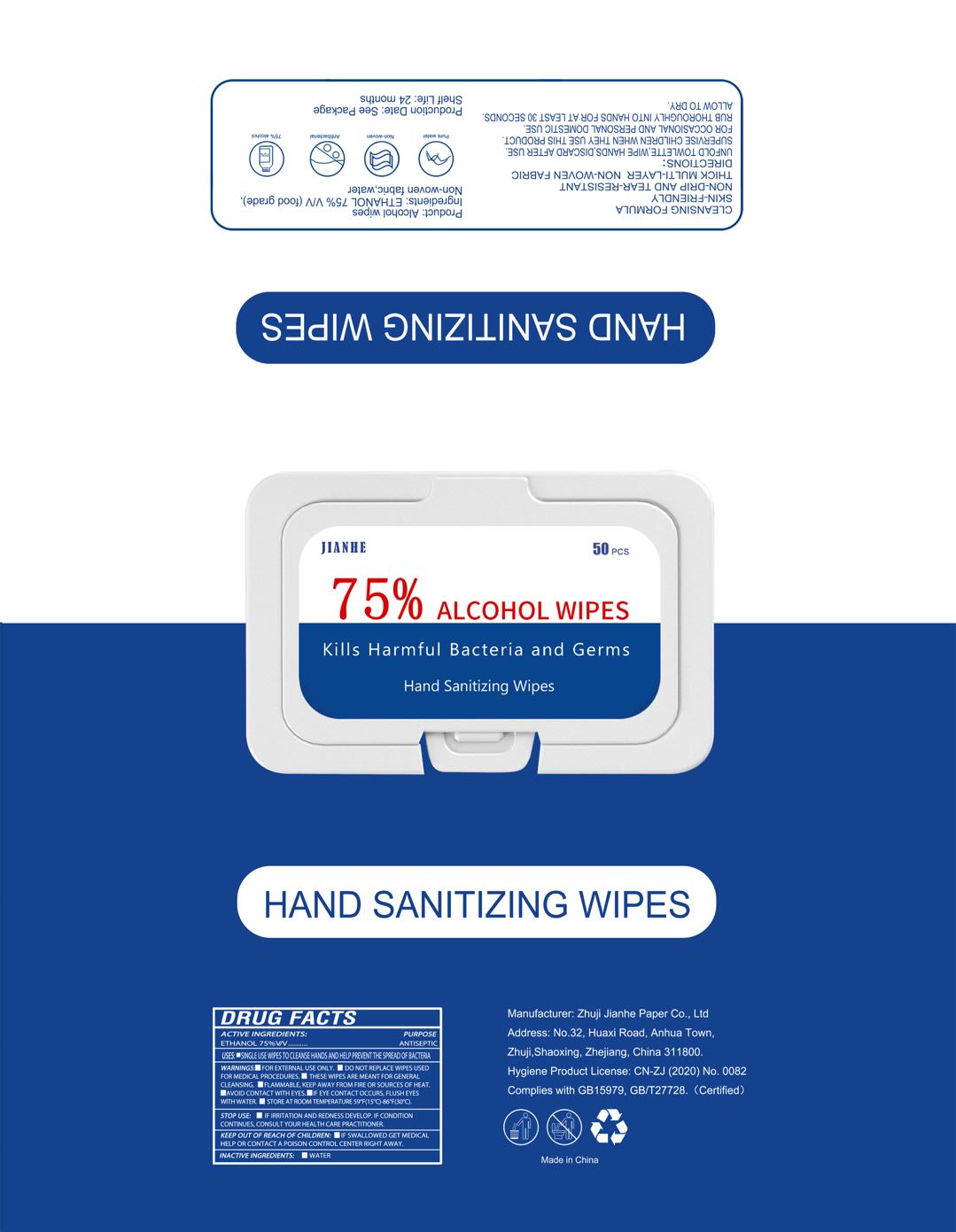 DRUG LABEL: Alcohol Wipes
NDC: 75163-101 | Form: CLOTH
Manufacturer: Zhuji Jianhe Paper Co., Ltd
Category: otc | Type: HUMAN OTC DRUG LABEL
Date: 20200803

ACTIVE INGREDIENTS: ALCOHOL 3.5 mL/1 1
INACTIVE INGREDIENTS: WATER

JianHe, Alcohol Wipes, 75% Ethanol

Active ingredient

Ethanol 75% v/v. Purpose: Antiseptic

Purpose

Antiseptic

WHEN USING

- Avoid contact with eyes.
- If eyes contact occurs, flush eyes with water.

- Do not replace wipes used for medical procedures.

Stop use

- If irritation and redness develop. If condition continues, consult your health care practitioner.

KEEP OUT OF REACH OF CHILDREN

If swallowed, get medical help or contact a Poison Control Center right away.

Uses

- Single use wipes to cleanse hands and help prevent the spread of bacteria
- These wipes are meant for general cleansing.

Directions

Unfold towlette, wipe hands, discard after use.

Supervise children when they use this product.

For occasional and personal domestic use.

Rub thoroughly into hands for at least 30 seconds. Allow to dry.

Warnings

For external use only.

Flammable, keep away from fire or sources of heat.

Other information

Store at room temperture 59℉(15℃)-86℉(30℃).

Inactive ingredients

- Water